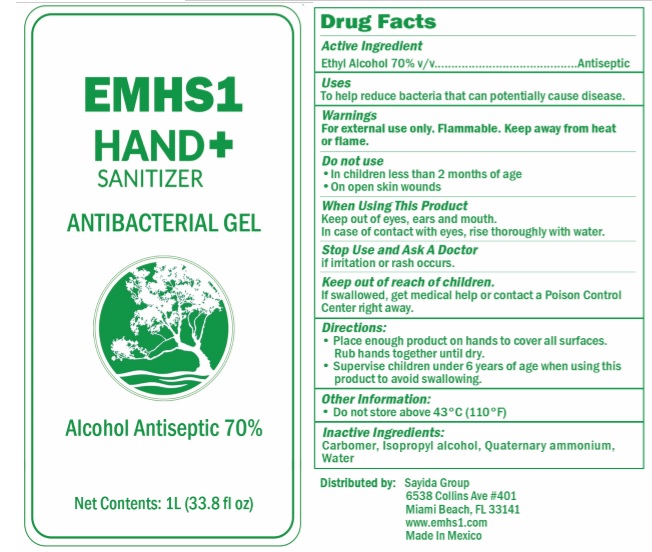 DRUG LABEL: EMHS1 Hand Sanitizer
NDC: 77858-0754 | Form: GEL
Manufacturer: Sayida Group LLC
Category: otc | Type: HUMAN OTC DRUG LABEL
Date: 20200616

ACTIVE INGREDIENTS: ALCOHOL 70 L/100 L
INACTIVE INGREDIENTS: CARBOMER HOMOPOLYMER, UNSPECIFIED TYPE; ISOPROPYL ALCOHOL; WATER

EMHS1 Hand Sanitizer (gel - 1L) bottle, pump NDC: 77858-0754-1
EMHS1 Hand Sanitizer (gel - 1L) bottle NDC: 77858-0754-2

Active Ingredient(s)

Ethyl Alcohol 70% v/v.

Purpose

Antiseptic

Use

To help reduce bacteria that can potentially cause disease.

Warnings

For external use only. Flammable. Keep away from heat or flame

Do not use

- in children less than 2 months of age
- on open skin wounds

When using this product keep out of eyes, ears, and mouth. In case of contact with eyes, rinse eyes thoroughly with water.

Stop use and ask a doctor if irritation or rash occurs.

Keep out of reach of children. If swallowed, get medical help or contact a Poison Control Center right away.

Directions

- Place enough product on hands to cover all surfaces. Rub hands together until dry.
- Supervise children under 6 years of age when using this product to avoid swallowing.

Other information

Do not store above 43C (110F)

Inactive ingredients

Carbomer, Isopropyl alcohol, Quaternary ammonium, Water

Package Label - Principal Display Panel

DISTRIBUTED BY: Sayida Group

6538 Collins Ave #401

Miami Beach, FL 33141

EMHS1 Hand Sanitizer (bottle, pump - 1L) NDC: 77858-0754-1

EMHS1 Hand Sanitizer (bottle - 1L) NDC: 77858-0754-2